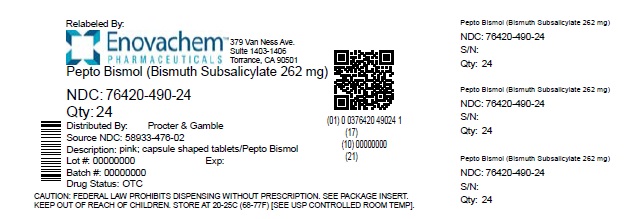 DRUG LABEL: Pepto-Bismol
NDC: 76420-490 | Form: TABLET
Manufacturer: ASCLEMED USA INC.
Category: otc | Type: HUMAN OTC DRUG LABEL
Date: 20251015

ACTIVE INGREDIENTS: BISMUTH SUBSALICYLATE 262 mg/1 1
INACTIVE INGREDIENTS: D&C RED NO. 27 ALUMINUM LAKE; CALCIUM CARBONATE; MAGNESIUM STEARATE; MANNITOL; CELLULOSE, MICROCRYSTALLINE; POLYSORBATE 80; SILICON DIOXIDE; SODIUM STARCH GLYCOLATE TYPE A POTATO

Pepto BISMOL®Caplets

Drug Facts

Active ingredient (in each caplet)

Bismuth subsalicylate 262 mg

Purpose

Upset stomach reliever and antidiarrheal

Uses

relieves

- travelers' diarrhea
- diarrhea
- upset stomach due to overindulgence in food and drink, including:
  - heartburn
  - indigestion
  - nausea
  - gas
  - belching
  - fullness

Warnings

Reye's syndrome:

Children and teenagers who have or are recovering from chicken pox or flu-like symptoms should not use this product. When using this product, if changes in behavior with nausea and vomiting occur, consult a doctor because these symptoms could be an early sign of Reye's syndrome, a rare but serious illness.

Allergy alert:

Contains salicylate. Do not take if you are

- allergic to salicylates (including aspirin)
- taking other salicylate products

Do not use if you have

- an ulcer
- a bleeding problem
- bloody or black stool

Ask a doctor before use if you have

- fever
- mucus in the stool

Ask a doctor or pharmacist before use if you are taking any drug for

- anticoagulation (thinning the blood)
- diabetes
- gout
- arthritis

When using this product a temporary, but harmless, darkening of the stool and/or tongue may occur

Stop use and ask a doctor if

- symptoms get worse or last more than 2 days
- ringing in the ears or loss of hearing occurs
- diarrhea lasts more than 2 days

PREGNANCY OR BREAST FEEDING

If pregnant or breast feeding, ask a health professional before use.

Keep out of reach of children. In case of overdose, get medical help or contact a Poison Control Center right away.

Directions

• swallow with water, do not chew
• adults and children 12 years and over:

- 2 caplets (1 dose) every ½ hour or 4 caplets (2 doses) every hour as needed for diarrhea
- 2 caplets (1 dose) every ½ hour as needed for overindulgence (upset stomach, heartburn, indigestion, nausea)

• do not exceed 8 doses (16 caplets) in 24 hours
• use until diarrhea stops but not more than 2 days
• children under 12 years: ask a doctor
• drink plenty of clear fluids to help prevent dehydration caused by diarrhea

Other information

- each caplet contains: calcium 27 mg
- salicylate 99 mg
- low sodium
- avoid excessive heat (over 104°F or 40°C)

Inactive ingredients

calcium carbonate, D&C red No. 27 aluminum lake, magnesium stearate, mannitol, microcrystalline cellulose, polysorbate 80, povidone, silicon dioxide, sodium starch glycolate

Questions?

1-800-717-3786

TAMPER EVIDENT: Do not use if inner printed seal on bottle is broken or missing.

Relabeled by:

Enovachem PHARMACEUTICALS

Torrance, CA 90501